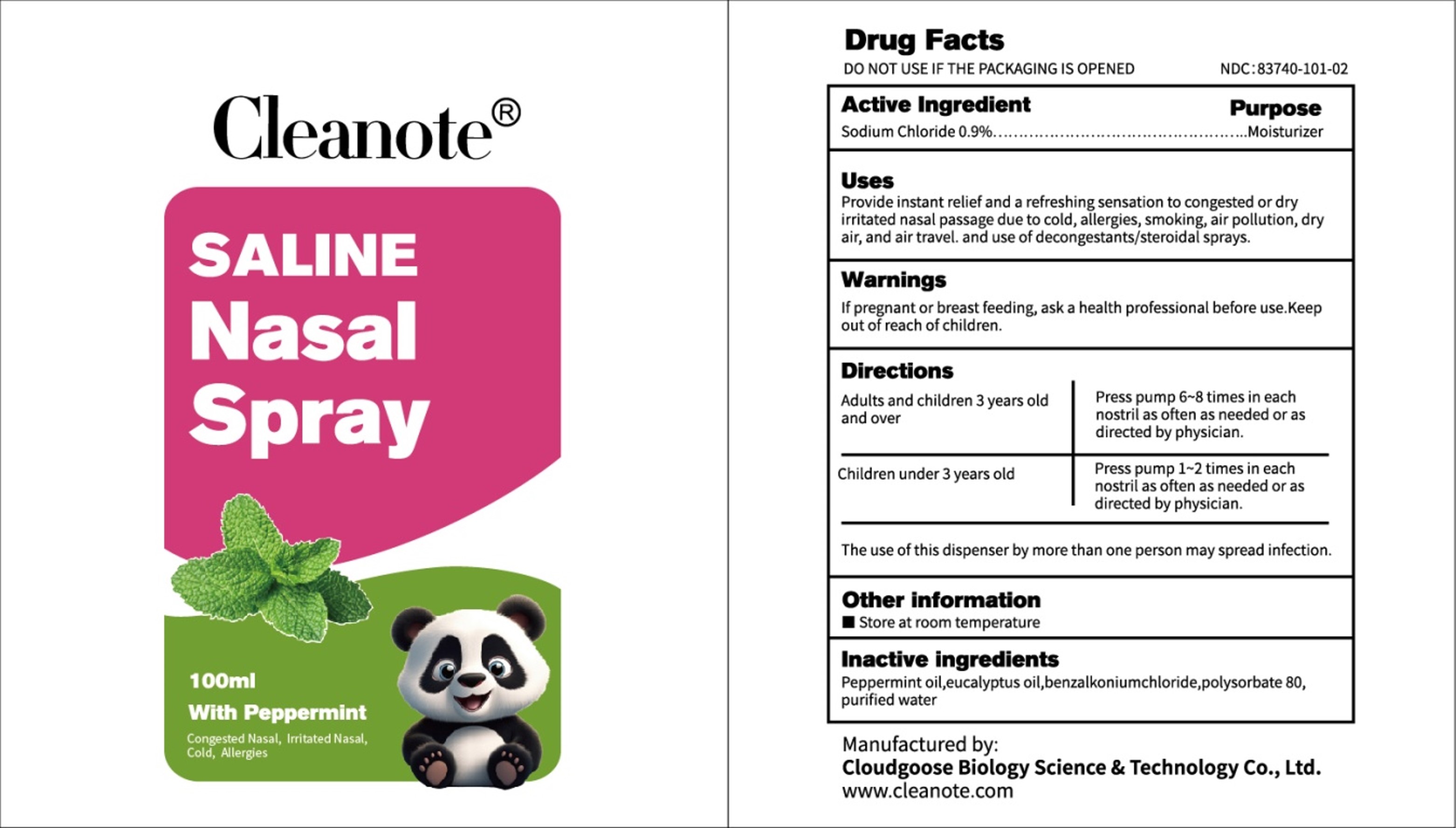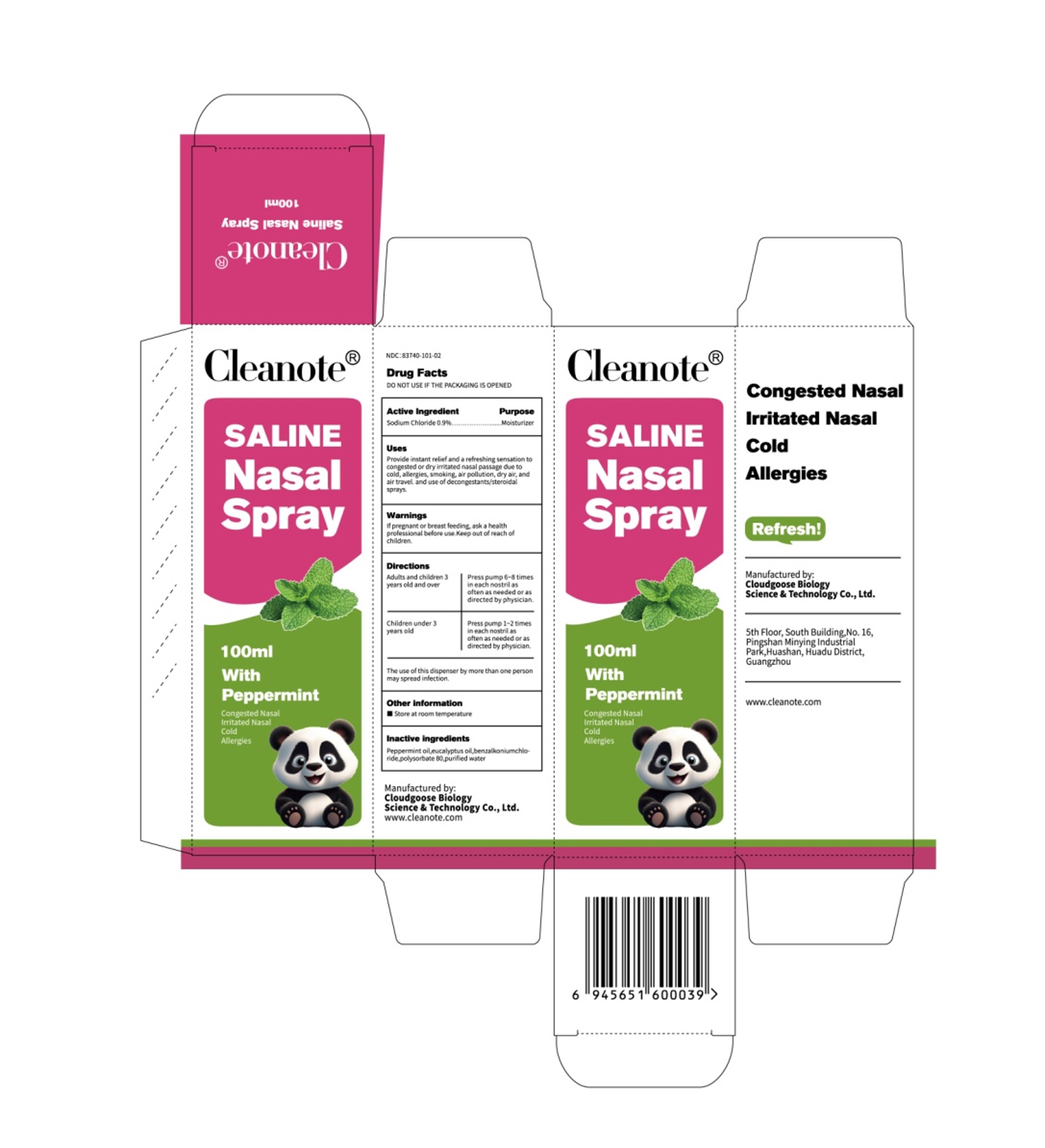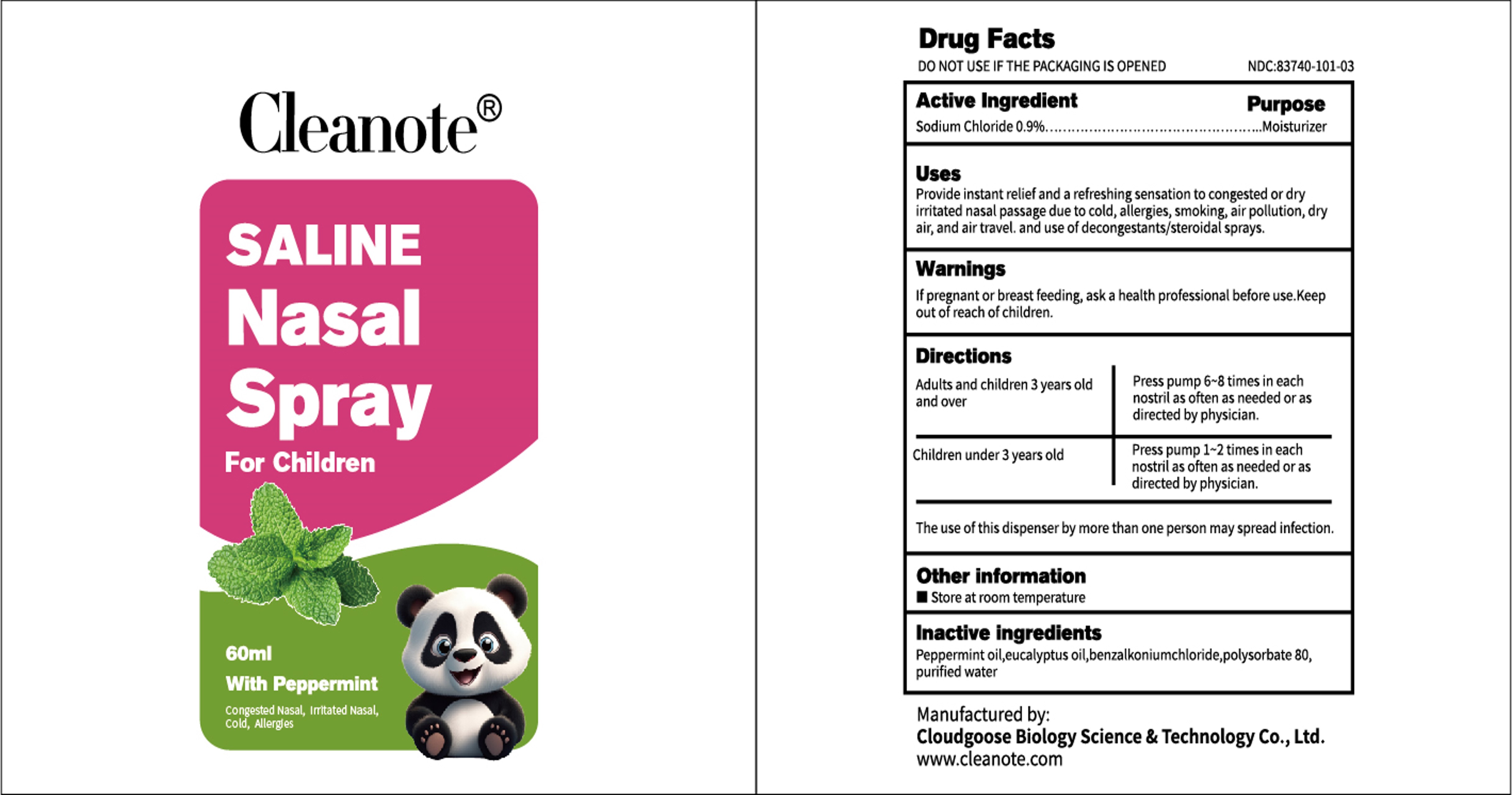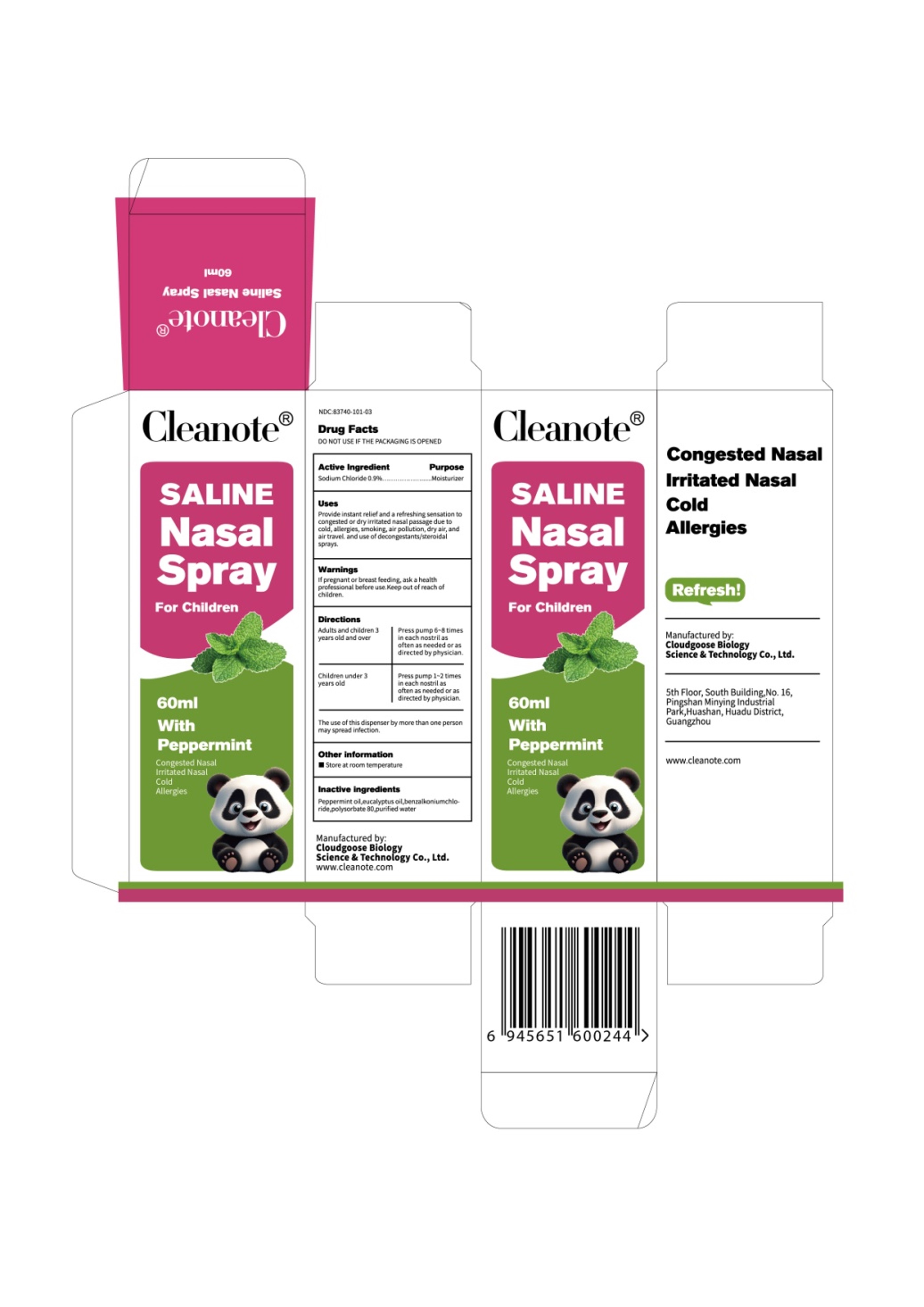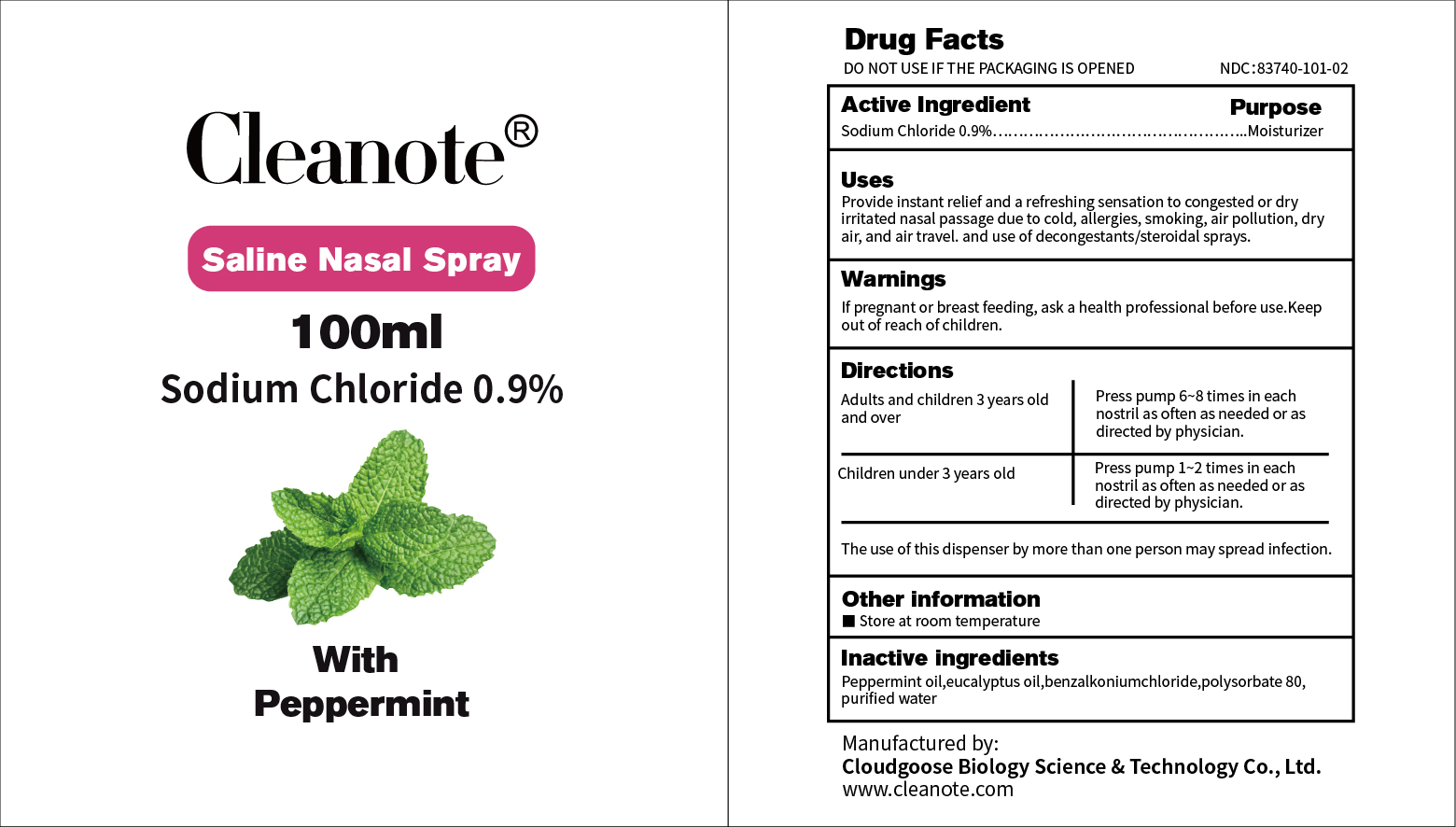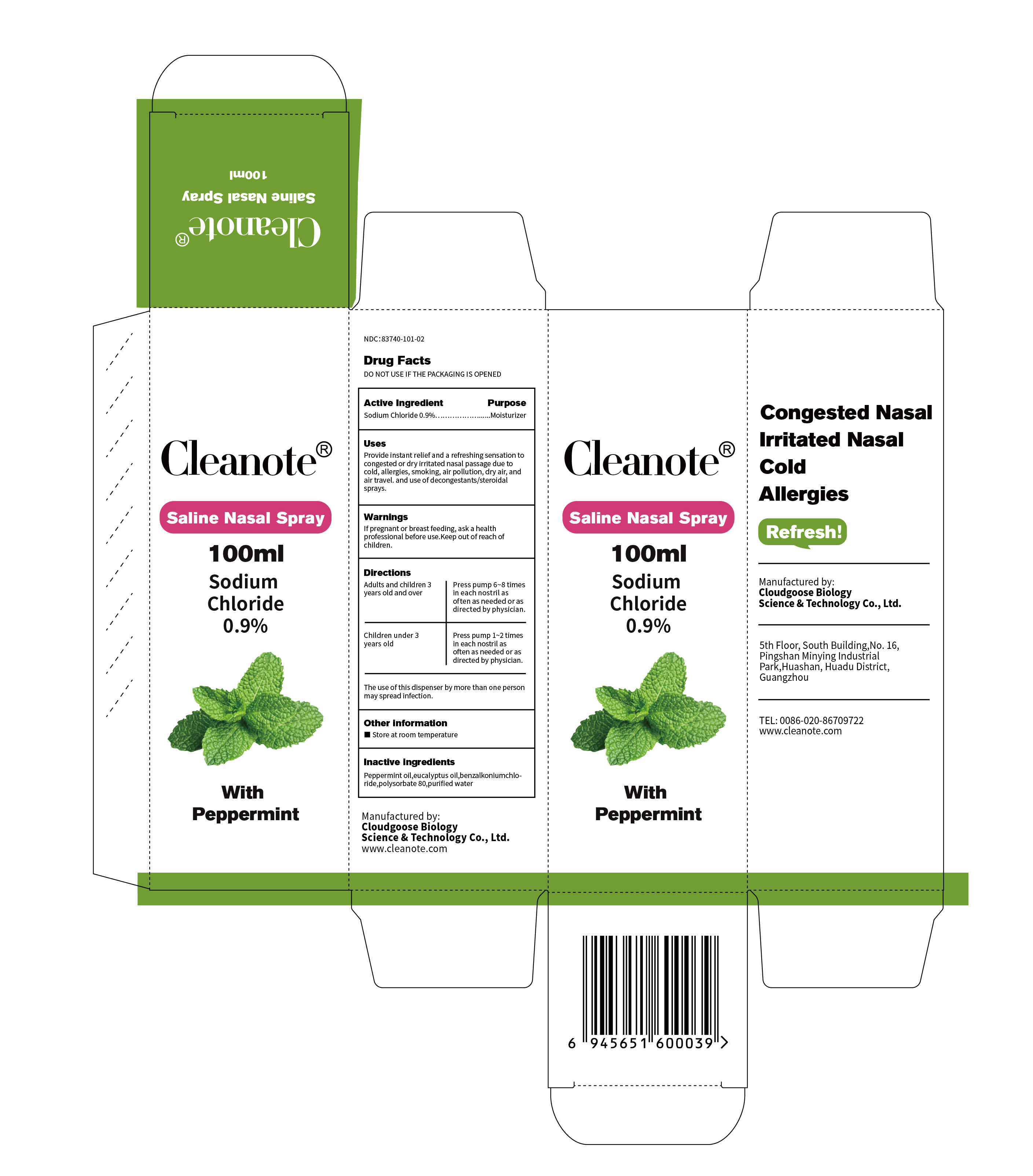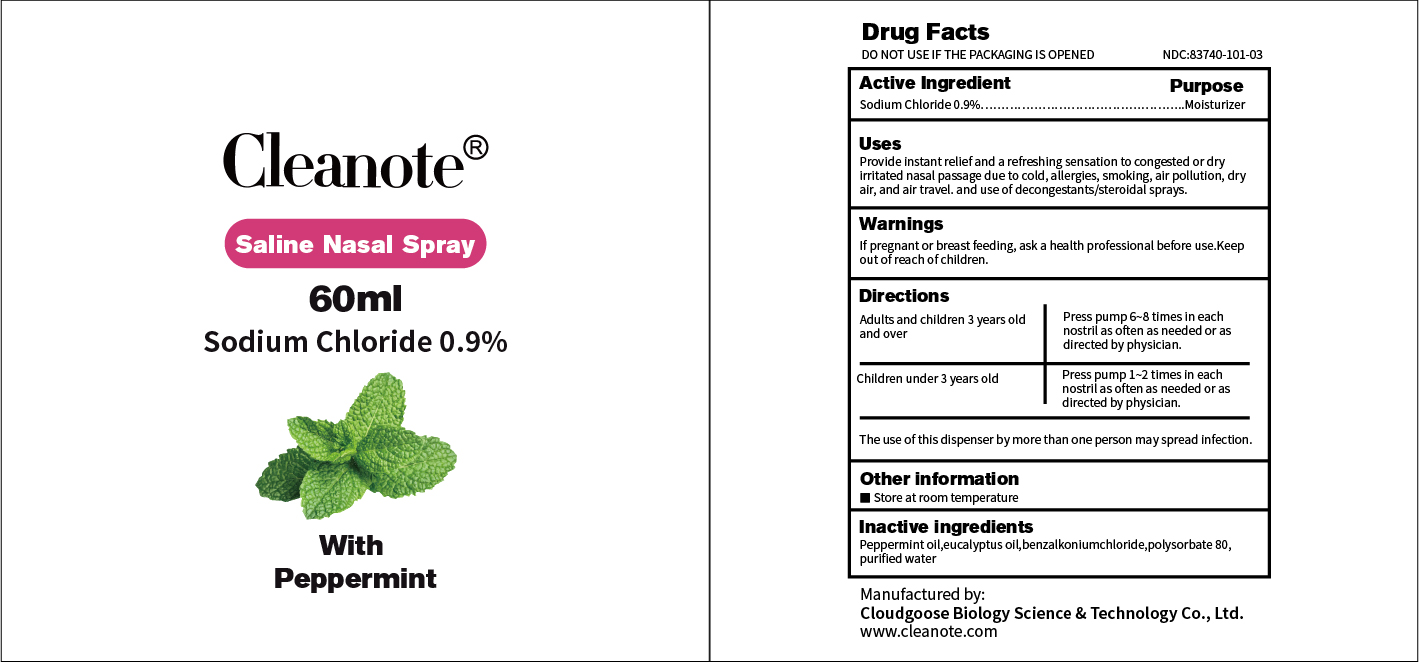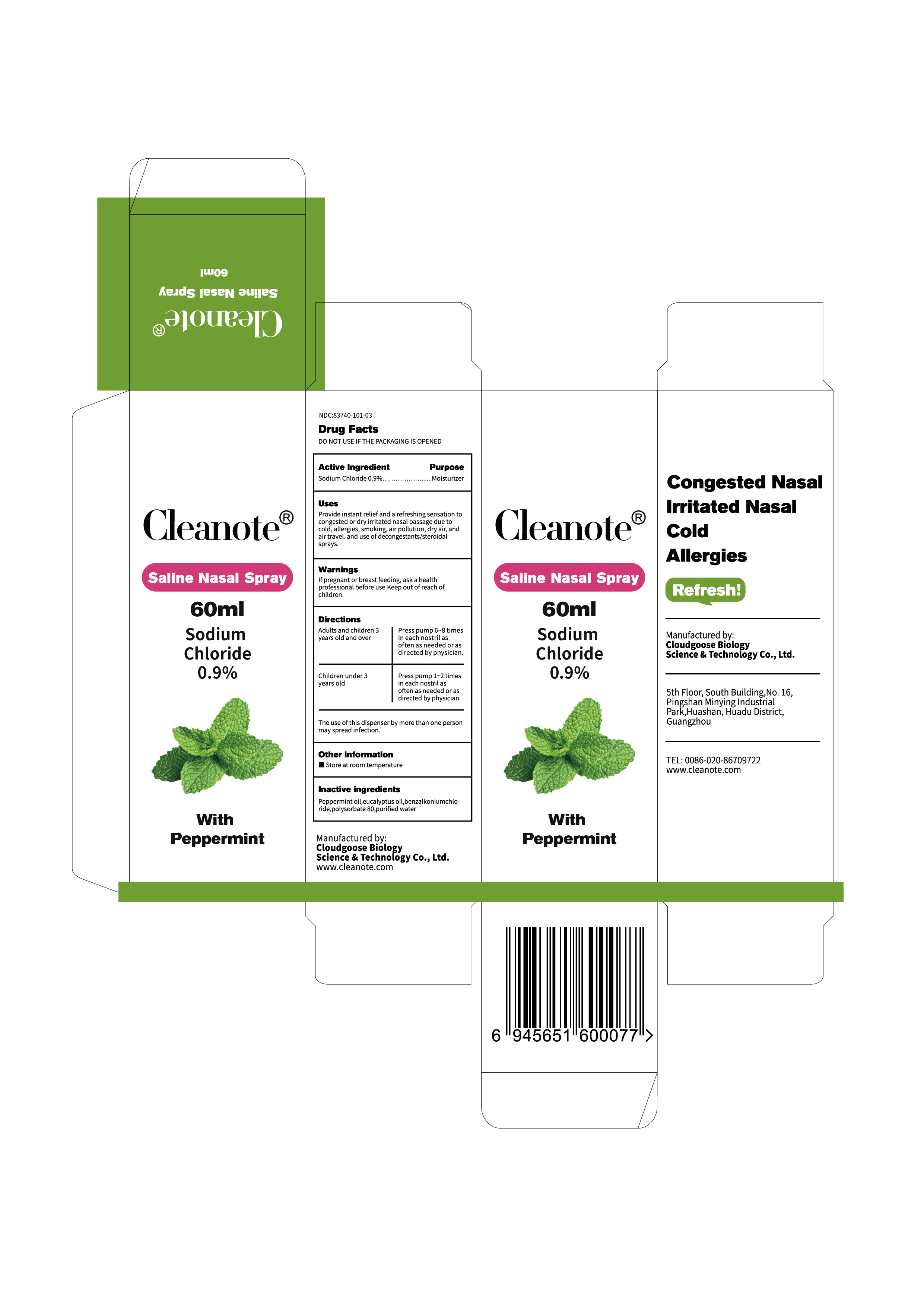 DRUG LABEL: Cleanote Saline Nasal Sprays
NDC: 83740-101 | Form: AEROSOL, SPRAY
Manufacturer: Cloudgoose Biology Science & Technology Co., Ltd.
Category: otc | Type: HUMAN OTC DRUG LABEL
Date: 20240126

ACTIVE INGREDIENTS: SODIUM CHLORIDE 9 mg/100 mL
INACTIVE INGREDIENTS: PEPPERMINT OIL; EUCALYPTUS OIL; BENZALKONIUM CHLORIDE; WATER; POLYSORBATE 80

Cleanote saline nasal spray

Cleanote saline nasal spray

ACTIVE INGREDIENT

Sodium Chloride 0.9%

PURPOSE

Provide instant relief and a refreshing sensation to congested or dryirritated nasal passage due to cold, allergies, smoking, air pollution, dryair, and air travel. and use of decongestants/steroidal sprays.

INDICATIONS AND USAGE

Provide instant relief and a refreshing sensation to congested or dryirritated nasal passage due to cold, allergies, smoking, air pollution, dryair, and air travel. and use of decongestants/steroidal sprays.

WARNINGS

lf pregnant or breast feeding, ask a health professional before use.Keep out of reach of children.

DO NOT USE

The use of this dispenser by more than one person may spread infection.

WHEN USING

adults and children 3 years oldand over.
press pump 6~8 times in eachnostril as often as needed or asdirected by physician.
children under 3 years old
press pump 1~2 times in eachnostril as often as needed or asdirected by physician.

STOP USE

lf pregnant or breast feeding, ask a health professional before use.

The use of this dispenser by more than one person may spread infection.

Keep out of reach of children.

DOSAGE AND ADMINISTRATION

adults and children 3 years oldand over.
press pump 6~8 times in eachnostril as often as needed or asdirected by physician.
children under 3 years old
press pump 1~2 times in eachnostril as often as needed or asdirected by physician.

STORAGE AND HANDLING

store at room temperature

INACTIVE INGREDIENT

Peppermint oil

Eucalyptus oil
Benzalkonium chloride
Polysorbate 80
Purified water